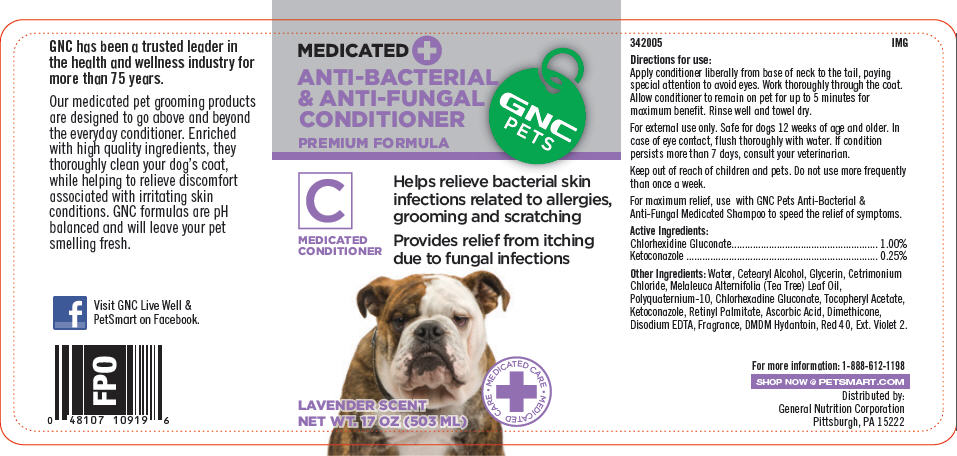 DRUG LABEL: GNC Pets Anti-Bacterial and Anti-Fungal Conditioner (Premium Formula)
NDC: 43655-005 | Form: SHAMPOO
Manufacturer: General Nutrition Corporation
Category: animal | Type: OTC ANIMAL DRUG LABEL
Date: 20181105

ACTIVE INGREDIENTS: Chlorhexidine Gluconate 10 mg/1 mL; Ketoconazole 2.5 mg/1 mL
INACTIVE INGREDIENTS: Water; Cetostearyl Alcohol; Glycerin; Cetrimonium Chloride; Tea Tree Oil; Polyquaternium-10 (400 MPA.S at 2%); .Alpha.-Tocopherol Acetate; Vitamin A Palmitate; Ascorbic Acid; Dimethicone; Edetate Disodium; DMDM Hydantoin; FD&C Red No. 40; Ext. D&C Violet No. 2

GNC Pets Anti-Bacterial & Anti-Fungal Conditioner (Premium Formula)

342005
IMG

INDICATIONS AND USAGE

Directions for use:

Apply conditioner liberally from base of neck to the tail, paying special attention to avoid eyes. Work thoroughly through the coat. Allow conditioner to remain on pet for up to 5 minutes for maximum benefit. Rinse well and towel dry.

For external use only. Safe for dogs 12 weeks of age and older. In case of eye contact, flush thoroughly with water. If condition persists more than 7 days, consult your veterinarian.

Keep out of reach of children and pets. Do not use more frequently than once a week.

For maximum relief, use with GNC Pets Anti-Bacterial & Anti-Fungal Medicated Shampoo to speed the relief of symptoms.

Active Ingredients:
Chlorhexidine Gluconate | 1.00%
Ketoconazole | 0.25%

Other Ingredients: Water, Cetearyl Alcohol, Glycerin, Cetrimonium Chloride, Melaleuca Alternifolia (Tea Tree) Leaf Oil, Polyquaternium-10, Chlorhexadine Gluconate, Tocopheryl Acetate, Ketoconazole, Retinyl Palmitate, Ascorbic Acid, Dimethicone, Disodium EDTA, Fragrance, DMDM Hydantoin, Red 40, Ext. Violet 2.

For more information: 1-888-612-1198

SHOP NOW @ PETSMART.COM

Distributed by:
General Nutrition Corporation
Pittsburgh, PA 15222

PRINCIPAL DISPLAY PANEL - 503 ML Bottle Label

MEDICATED +
ANTI-BACTERIAL
& ANTI-FUNGAL
CONDITIONER

PREMIUM FORMULA

GNC
PETS

C
MEDICATED
CONDITIONER

Helps relieve bacterial skin
infections related to allergies,
grooming and scratching

Provides relief from itching
due to fungal infections

• MEDICATED CARE
+
• MEDICATED CARE

LAVENDER SCENT
NET WT. 17 OZ (503 ML)